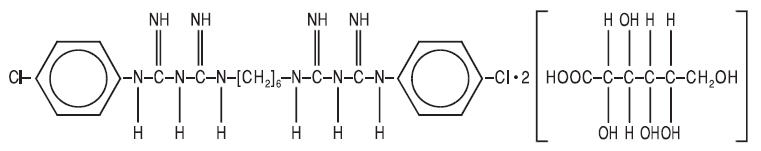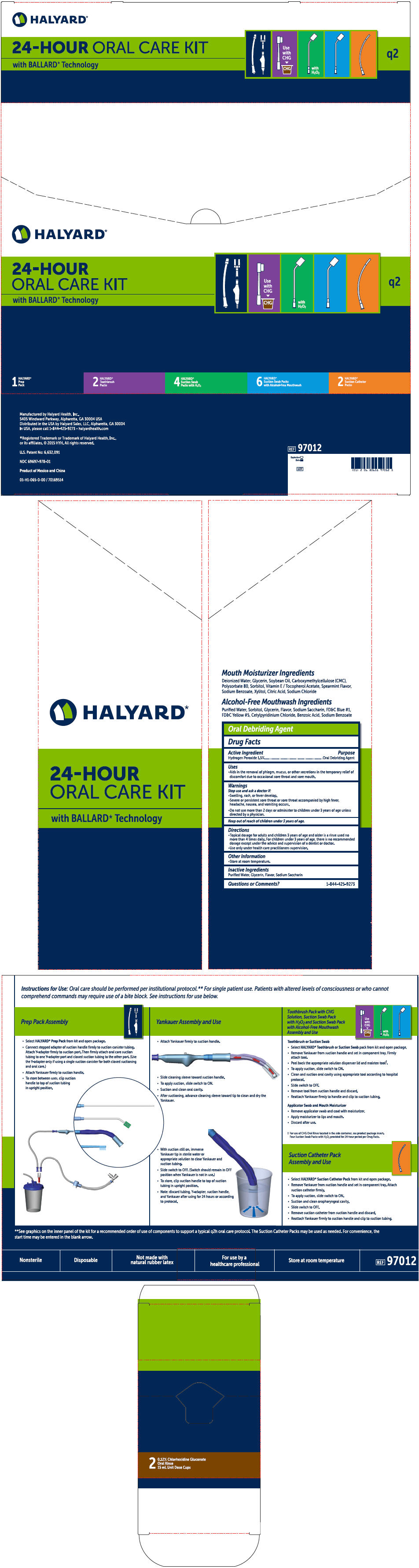 DRUG LABEL: Q2 Oral Care Kit with CHG
NDC: 69697-982 | Form: KIT | Route: ORAL
Manufacturer: Halyard Health
Category: prescription | Type: HUMAN PRESCRIPTION DRUG LABEL
Date: 20160127

ACTIVE INGREDIENTS: Hydrogen peroxide 0.015 mg/1 mL; Chlorhexidine Gluconate 1.2 mg/1 mL
INACTIVE INGREDIENTS: Water; Glycerin; Mint; Saccharin Sodium Dihydrate; Alcohol; FD&C Blue no. 1; Glycerin; PEG-40 sorbitan diisostearate; Mint; Saccharin Sodium Dihydrate; Water

Halyard
24-Hour Oral Care Kit Q2

Oral Debriding Agent

Drug Facts

Active Ingredient

Hydrogen Peroxide 1.5%

Purpose

Oral Debriding Agent

Uses

- Aids in the removal of phlegm, mucus, or other secretions in the temporary relief of discomfort due to occasional sore throat and sore mouth.

Warnings

Stop use and ask a doctor if:

- Swelling, rash, or fever develop.
- Severe or persistent sore throat or sore throat accompanied by high fever, headache, nausea, and vomiting occurs.

- Do not use more than 2 days or administer to children under 3 years of age unless directed by a physician.

Keep out of reach of children under 3 years of age.

Directions

- Topical dosage for adults and children 3 years of age and older is a rinse used no more than 4 times daily. For children under 3 years of age, there is no recommended dosage except under the advice and supervision of a dentist or doctor.
- Use only under health care practitioners supervision.

Other Information

- Store at room temperature.

Inactive Ingredients

Purified Water, Glycerin, Flavor, Sodium Saccharin

Questions or Comments?

1-844-425-9273

CHLORHEXIDINE GLUCONATE ORAL RINSE, 0.12%

Rx Only

DESCRIPTION

Chlorhexidine Gluconate Oral Rinse, 0.12% is an oral rinse containing 0.12% chlorhexidine gluconate (1, 1'-hexamethylene bis[5-(p-chlorophenyl) biguanide] di-D-gluconate) in a base containing 11.6% v/v alcohol, FD&C Blue No. 1, glycerin, PEG-40 sorbitan diisostearate, peppermint flavor, sodium saccharin, and purified water. Chlorhexidine Gluconate Oral Rinse is a near-neutral solution (pH range 5-7). Chlorhexidine gluconate is a salt of chlorhexidine and gluconic acid. Its structural formula is: C22H30Cl2N10•2C6H12O7 MW = 897.8

CLINICAL PHARMACOLOGY

Chlorhexidine Gluconate Oral Rinse, 0.12% provides antimicrobial activity during oral rinsing. The clinical significance of 0.12% chlorhexidine gluconate oral rinse's anti-microbial activities is not clear. Microbiological sampling of plaque has shown a general reduction of counts of certain assayed bacteria, both aerobic and anaerobic, ranging from 54-97% through six months use. Use of chlorhexidine gluconate oral rinse in a six month clinical study did not result in any significant changes in bacterial resistance, overgrowth of potentially opportunistic organisms or other adverse changes in the oral microbial ecosystem. Three months after chlorhexidine gluconate use was discontinued, the number of bacteria in plaque had returned to baseline levels and resistance of plaque bacteria to chlorhexidine gluconate was equal to that at baseline.

PHARMACOKINETICS

Pharmacokinetic studies with a 0.12% chlorhexidine gluconate oral rinse indicate approximately 30% of the active ingredient, chlorhexidine gluconate, is retained in the oral cavity following rinsing. This retained drug is slowly released into the oral fluids. Studies conducted on human subjects and animals demonstrate chlorhexidine gluconate is poorly absorbed from the gastrointestinal tract. The mean plasma level of chlorhexidine gluconate reached a peak of 0.206 µg/g in humans 30 minutes after they ingested a 300-mg dose of the drug. Detectable levels of chlorhexidine gluconate were not present in the plasma of these subjects 12 hours after the compound was administered. Excretion of chlorhexidine gluconate occurred primarily through the feces (~90%). Less than 1% of the chlorhexidine gluconate ingested by these subjects was excreted in the urine.

INDICATIONS AND USAGE

16 oz. Chlorhexidine Gluconate Oral Rinse, 0.12% - Chlorhexidine Gluconate Oral Rinse, 0.12% is indicated for use between dental visits as part of a professional program for the treatment of gingivitis as characterized by redness and swelling of the gingivae, including gingival bleeding upon probing. Chlorhexidine Gluconate Oral Rinse, 0.12% has not been tested among patients with acute necrotizing ulcerative gingivitis (ANUG). For patients having coexisting gingivitis and periodontitis, see PRECAUTIONS.

CONTRAINDICATIONS

Chlorhexidine Gluconate Oral Rinse, 0.12% should not be used by persons who are known to be hypersensitive to chlorhexidine gluconate or other formula ingredients.

WARNINGS

The effect of Chlorhexidine Gluconate Oral Rinse, 0.12% on periodontitis has not been determined. An increase in supragingival calculus was noted in clinical testing in users of chlorhexidine gluconate oral rinse compared with control users. It is not known if chlorhexicine gluconate use results in an increase in subgingival calculus. Calculus deposits should be removed by a dental prophylaxis at intervals not greater than six months. Hypersensitivity and generalized allergic reactions have occurred. See CONTRAINDICATIONS.

PRECAUTIONS

General

1. For patients having coexisting gingivitis and periodontitis, the presence or absence of gingival inflammation following treatment with Chlorhexidine Gluconate Oral Rinse, 0.12% should not be used as a major indicator of underlying periodontitis.
2. Chlorhexidine Gluconate Oral Rinse, 0.12% can cause staining of oral surfaces, such as tooth surfaces, restorations, and the dorsum of the tongue. Not all patients will experience a visually significant increase in toothstaining. In clinical testing, 56% of chlorhexidine gluconate oral rinse users exhibited a measurable increase in facial anterior stain, compared to 35% of control users after six months; 15% of chlorhexidine gluconate users developed what was judged to be heavy stain, compared to 1% of control users after six months. Stain will be more pronounced in patients who have heavier accumulations of unremoved plaque. Stain resulting from use of Chlorhexidine Gluconate Oral Rinse, 0.12% does not adversely affect health of the gingivae or other oral tissues. Stain can be removed from most tooth surfaces by conventional professional prophylactic techniques. Additional time may be required to complete the prophylaxis. Discretion should be used when prescribing to patients with anterior facial restorations with rough surfaces or margins. If natural stain cannot be removed from these surfaces by a dental prophylaxis, patients should be excluded from Chlorhexidine Gluconate Oral Rinse, 0.12% treatment if permanent discoloration is unacceptable. Stain in these areas may be difficult to remove by dental prophylaxis and on rare occasions may necessitate replacement of these restorations.
3. Some patients may experience an alteration in taste perception while undergoing treatment with chlorhexidine gluconate oral rinse. Rare instances of permanent taste alteration following chlorhexidine gluconate oral rinse have been reported via post-marketing product surveillance.

Pregnancy

Teratogenic Effects

Pregnancy Category B

Reproduction studies have been performed in rats and rabbits at chlorhexidine gluconate doses up to 300 mg/kg/day and 40 mg/kg/day, respectively, and have not revealed evidence of harm to fetus. However, adequate and well-controlled studies in pregnant women have not been done. Because animal reproduction studies are not always predictive of human response, this drug should be used during pregnancy only if clearly needed.

Nursing Mothers

It is not known whether this drug is excreted in human milk. Because many drugs are excreted in human milk, caution should be exercised when Chlorhexidine Gluconate Oral Rinse, 0.12% is administered to nursing women.

In parturition and lactation studies with rats, no evidence of impaired parturition or of toxic effects to suckling pups was observed when chlorhexidine gluconate was administered to dams at doses that were over 100 times greater than that which would result from a person's ingesting 30 ml (2 capfuls) of chlorhexidine gluconate oral rinse, 0.12% per day.

Pediatric Use

Clinical effectiveness and safety of Chlorhexidine Gluconate Oral Rinse, 0.12% have not been established in children under the age of 18

Carcinogenesis, Mutagenesis, and Impairment of Fertility

In a drinking water study in rats, carcinogenic effects were not observed at doses up to 38 mg/kg/day. Mutagenic effects were not observed in two mammalian in vivo mutagenesis studies with chlorhexidine gluconate. The highest doses of chlorhexidine used in a mouse dominant-lethal assay and a hamster cytogenetics test were 1000 mg/kg/day and 250 mg/kg/day, respectively. No evidence of impaired fertility was observed in rats at doses up to 100 mg/kg/day.

ADVERSE REACTIONS

The most common side effects associated with chlorhexidine gluconate oral rinses are: 1) an increase in staining of teeth and other oral surfaces; 2) an increase in calculus formation; and 3) an alteration in taste perception, see WARNINGS and PRECAUTIONS. Oral irritation and local allergy-type symptoms have been spontaneously reported as side effects associated with use of chlorhexidine gluconate rinse.

The following oral mucosal side effects were reported during placebo-controlled adult clinical trials: aphthous ulcer, grossly obvious gingivitis, trauma, ulceration, erythema, desquamation, coated tongue, keratinization, geographic tongue, mucocele, and short frenum. Each occurred at a frequency of less than 1.0%. Among post marketing reports, the most frequently reported oral mucosal symptoms associated with chlorhexidine gluconate oral rinse, 0.12% are stomatitis, gingivitis, glossitis, ulcer, dry mouth, hypesthesia, glossal edema, and paresthesia.

Minor irritation and superficial desquamation of the oral mucosa have been noted in patients using chlorhexidine gluconate oral rinse, 0.12%.

There have been cases of parotid gland swelling and inflammation of the salivary glands (sialadentis) reported in patients using chlorhexidine gluconate oral rinse.

To report SUSPECTED ADVERSE REACTIONS, contact Hi-Tech Pharmacal Co., Inc. at 1-800-262-9010 or FDA at 1-800-FDA-1088 or www.fda.gov/medwatch.

OVERDOSAGE

Ingestion of 1 or 2 ounces of Chlorhexidine Gluconate Oral Rinse, 0.12% by a small child (~10 kg body weight) might result in gastric distress, including nausea, or signs of alcohol intoxication. Medical attention should be sought if more than 4 ounces of Chlorhexidine Gluconate Oral Rinse, 0.12% is ingested by a small child or if signs of alcohol intoxication develop.

DOSAGE AND ADMINISTRATION

Chlorhexidine Gluconate Oral Rinse, 0.12% therapy should be initiated directly following a dental prophylaxis. Patients using Chlorhexidine Gluconate Oral Rinse, 0.12% should be reevaluated and given a thorough prophylaxis at intervals no longer than six months.

Recommended use is twice daily oral rinsing for 30 seconds, morning and evening after toothbrushing. Usual dosage is 1/2 fl oz (marked in cup) of undiluted Chlorhexidine Gluconate Oral Rinse, 0.12%. Patients should be instructed to not rinse with water or other mouthwashes, brush teeth or eat immediately after using Chlorhexidine Gluconate Oral Rinse, 0.12%. Chlorhexidine Gluconate Oral Rinse, 0.12% is not intended for ingestion and should be expectorated after rinsing.

HOW SUPPLIED

Chlorhexidine Gluconate Oral Rinse, 0.12% is a blue, peppermint flavored liquid in:

A 16 fl oz (473 mL) amber plastic bottle with a child-resistant closure and dosage cup for consumer use, and in 15 mL unit dose cups.

It should be dispensed in original container or in amber glass.

STORAGE AND HANDLING

Store above freezing 0°C (32°F).

Rx only

Manufactured by:
Hi-Tech
Pharmacal Co., Inc.
Amityville, NY 11701

Rev. 720:00 7/10
MG# 11387

PRINCIPAL DISPLAY PANEL - Kit Carton

HALYARD*

24-HOUR
ORAL CARE KIT
with BALLARD* Technology

Use
with
CHG
▼
CHG

with
H2O2

q2

1
HALYARD*
Prep
Pack

2
HALYARD*
Toothbrush
Packs

4
HALYARD*
Suction Swab
Packs with H2O2

6
HALYARD*
Suction Swab Packs
with Alcohol-Free Mouthwash

2
HALYARD*
Suction Catheter
Packs